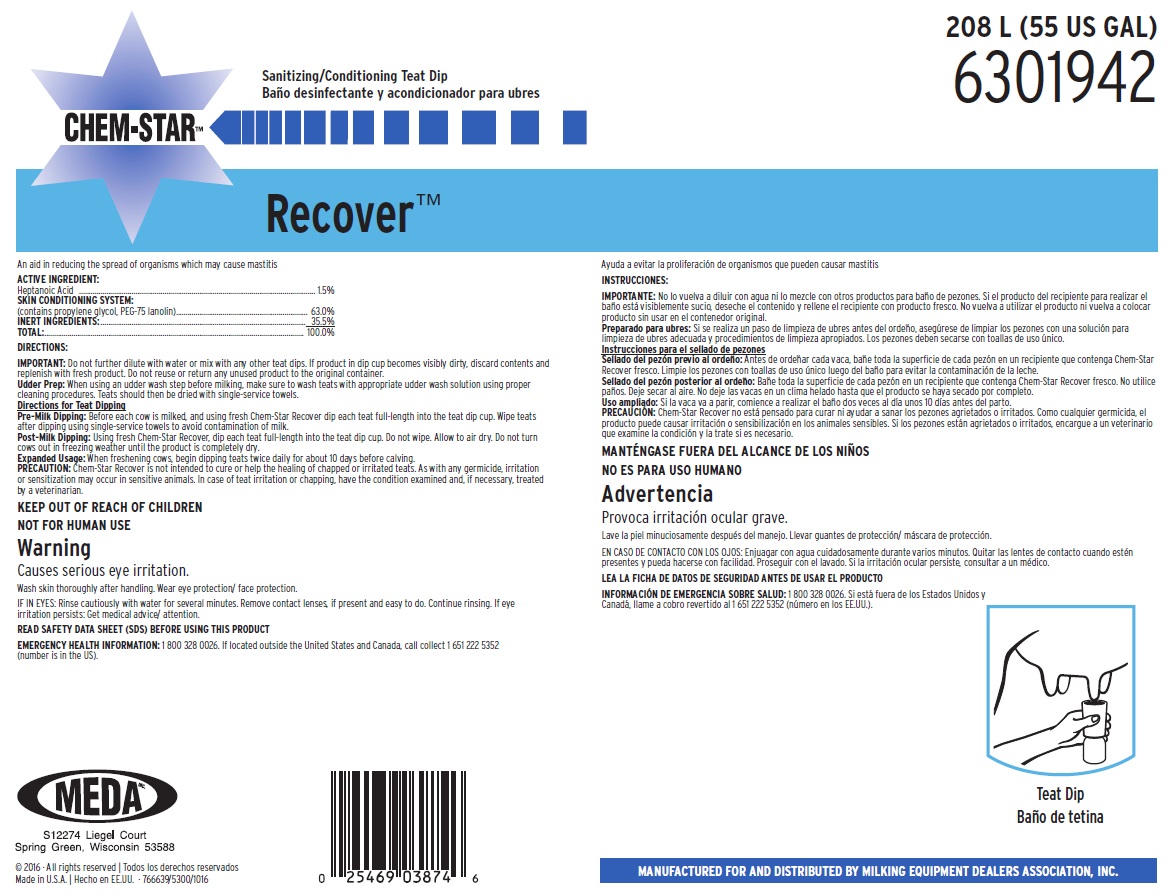 DRUG LABEL: Chem-Star Recover
NDC: 59511-411 | Form: SOLUTION
Manufacturer: MEDA Inc. 
Category: animal | Type: OTC ANIMAL DRUG LABEL
Date: 20170110

ACTIVE INGREDIENTS: HEPTANOIC ACID 15 mg/1 mL
INACTIVE INGREDIENTS: GLYCERIN; PROPYLENE GLYCOL; WATER

KEEP OUT OF REACH OF CHILDREN

NOT FOR HUMAN USE

Warning

Causes serious eye irritation

Wash skin thoroughly after handling. Wear eye protection/ face protection.

IF IN EYES: Rinse cautiously with water for several minutes. Remove contact lenses, if present and easy to do. Continue rinsing. If eye irritation persists: Get medical advice/ attention.

DIRECTIONS:

IMPORTANT: Do not further dilute with water or mix with any other teat dips. If product in dip cup becomes visibly dirty, discard contents and replenish with fresh product. Do not reuse or return any unused product to the original container.

Udder Prep: When using an udder wash step before milking, make sure to wash teats with appropriate udder wash solution using proper cleaning procedures. Teats should then be dried with single-service towels.

Directions for Teat Dipping

Pre-Milk Dipping: Before each cow is milked, and using fresh Chem-Star Recover dip each teat full-length into the teat dip cup. Wipe teats after dipping using single-service towels to avoid contamination of milk.

Post-Milk Dipping: Using fresh Chem-Star Recover, dip each teat full-length into the teat dip cup. Do not wipe. Allow to air dry. Do not turn cows out in freezing weather until the product is completely dry.

Expanded Usage: When freshening cows, begin dipping teats twice daily for about 10 days before calving.

PRECAUTION: Chem-Star Recover is not intended to cure or help the healing of chapped or irritated teats. As with any germicide, irritation or sensitization may occur in sensitive animals. In case of teat irritation or chapping, have the condition examined and, if necessary, treated by a veterinarian.

OTHER SAFETY INFORMATION

READ SAFETY DATA SHEET (SDS) BEFORE USING THIS PRODUCT

EMERGENCY HEALTH INFORMATION: 1 800 328 0026. If located outside the United States and Canada, call collect 1 651 222 5352 (number is in the US).

PACKAGE LABEL

208 L (55 US GAL)

6301942

Sanitizing/Conditioning Teat Dip

CHEM-STAR™

Recover ™

An Aid in Reducing the Spread of Organisms Which May Cause Mastitis

ACTIVE INGREDIENT:

Heptanoic Acid ................................................1.5%

SKIN CONDITIONING SYSTEM:

(contains propylene glycol, PEG-75 lanolin)........ 63.0%

INERT INGREDIENTS:................................... 35.5%

TOTAL:......................................................... 100.0%

MEDA

S12274 Liegel Court

Sprint Green, Wisconsin 53588

MANUFACTURED FOR AND DISTRIBUTED BY MILKING EQUIPMENT DEALERS ASSOCIATION, INC.

© 2016 All Rights Reserved

Made in U.S.A. 766639/5300/1016